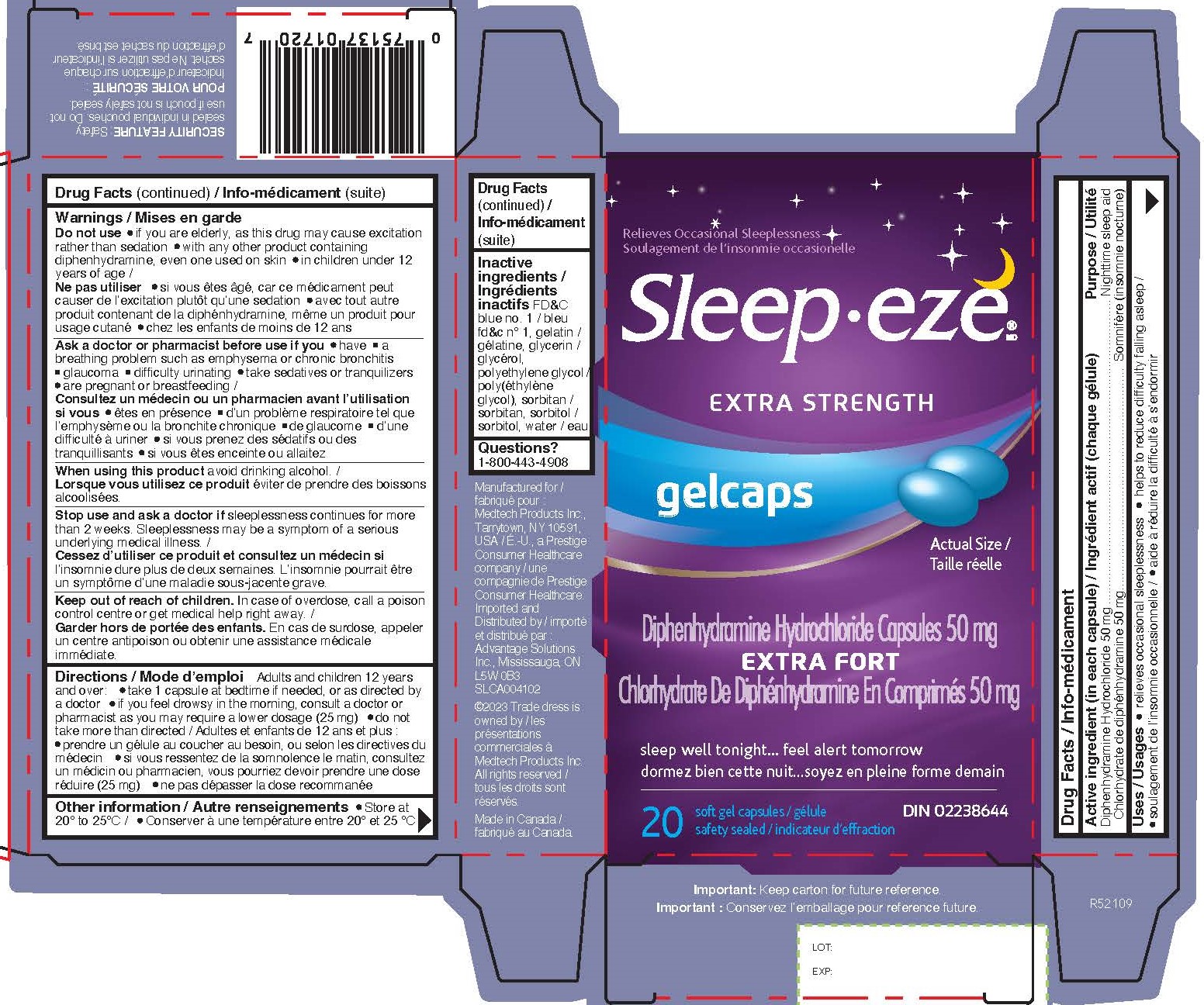 DRUG LABEL: Diphenhydramine Hydrochloride
NDC: 10267-5217 | Form: CAPSULE, LIQUID FILLED
Manufacturer: Contract Pharmcal Corp.
Category: otc | Type: HUMAN OTC DRUG LABEL
Date: 20231201

ACTIVE INGREDIENTS: DIPHENHYDRAMINE HYDROCHLORIDE 50 mg/1 1
INACTIVE INGREDIENTS: FD&C BLUE NO. 1; GELATIN; GLYCERIN; POLYETHYLENE GLYCOL 400; SORBITAN; SORBITOL; WATER

5217- Export